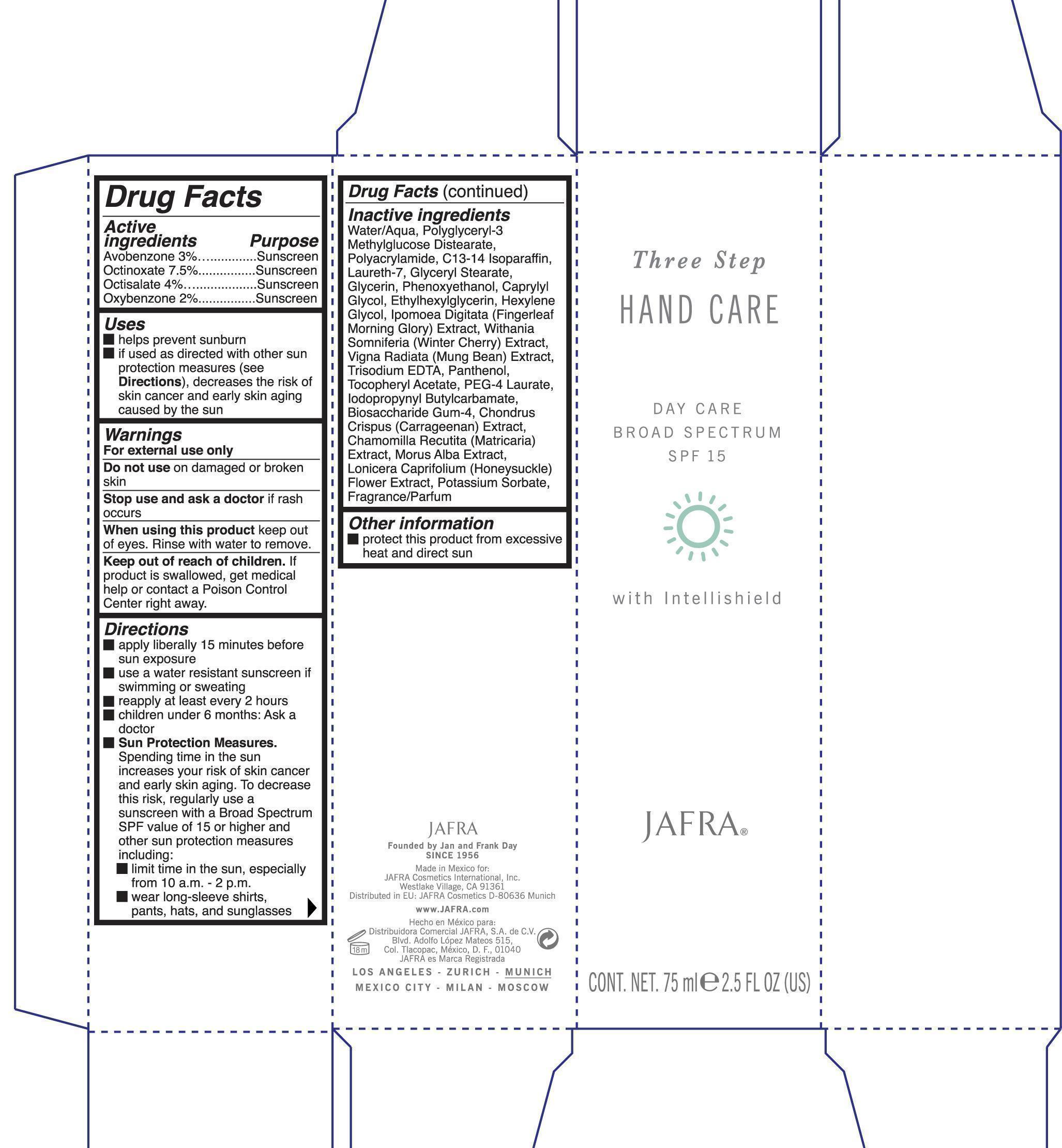 DRUG LABEL: Hand Care Day care Broad Spectrum SPF 15
NDC: 68828-118 | Form: LOTION
Manufacturer: Jafra Cosmetics International Inc
Category: otc | Type: HUMAN OTC DRUG LABEL
Date: 20190522

ACTIVE INGREDIENTS: AVOBENZONE 3 g/100 mL; OCTINOXATE 7.5 g/100 mL; OCTISALATE 4 g/100 mL; OXYBENZONE 2 g/100 mL
INACTIVE INGREDIENTS: WATER; POLYACRYLAMIDE (1500 MW); C13-14 ISOPARAFFIN; LAURETH-7; GLYCERYL MONOSTEARATE; GLYCERIN; PHENOXYETHANOL; CAPRYLYL GLYCOL; ETHYLHEXYLGLYCERIN; HEXYLENE GLYCOL; MUNG BEAN; EDETATE TRISODIUM; PANTHENOL; .ALPHA.-TOCOPHEROL ACETATE; PEG-4 LAURATE; IODOPROPYNYL BUTYLCARBAMATE; CHONDRUS CRISPUS; LONICERA CAPRIFOLIUM FLOWER; POTASSIUM SORBATE

Day Care Broad Spectrum SPF 15

Active Ingredients Purpose

Avobenzone 3% Sunscreen

Octinoxate 7.5% Sunscreen

Octisalate 4% Sunscreen

Oxybenzone 2% Sunscreen

Uses

helps prevent sunburn

If used as directed with other sun with other sun protection measures (see Directions), decreases the risk of skin cancer and early skin aging caused by the sun.

Keep out of reach of children. If product is swallowed, get medical help or contact a Poison Control Center right away.

Stop use and ask a doctor if rash occurs

Warnings

For external use only

Do not use on damaged or broken skin

When using this product keep out of eyes. Rinse with water to remove.

Directions

apply liberally 15 minutes before sun exposure

use a water resistant sunscreen if swimming or sweating

reapply at least every two hours

children under 6 months: Ask a doctor

Sun Protection Measures.

Spending time in the sun increases your risk of skin cancer and early skin aging. To decrease this regularly use a sunscreen with a broad spectrum SPF value of 15 or higher and other sun protection measures including:

limit time in the sun, especially from 10 a.m. - 2 p.m.

wear long-sleeve shirts, pants, hats, and sunglasses

INACTIVE INGREDIENT

Water/Aqua, Polyglyceryl-3 Methylglucose Distearate, Polyacrylamide, C13-14 Isoparaffin, Laureth-7, Glyceryl Stearate, Glycerin, Phenoxyethanol, Caprylyl Glycol, Ethylhexylglycerin, Hexylene Glycol, Ipomoea Digitata (Fingerleaf Morning Glory) Extract, Withania Somniferia (Winter Cherry) Extract, Vigna Radiata (Mung Bean) Extract, Trisodium EDTA, Panthenol, Tocopheryl Acetate, PEG-4 Laurate, Iodopropynyl Butylcarbamate, Biosaccharide Gum-4, Chondrus Crispus (Carrageenan) Extract, Chamomilla Recutita (Matricaria) Extract(MATRICARIA RECUTITA), Morus Alba Extract, Lonicera Caprifolium (Honeysuckle) Flower Extract, Potassium Sorbate, Fragrance/Parfum

PACKAGE LABEL

Three Step Hand Care

Day Care Broad Spectrum SPF 15 with intellishield

Jafra

Cont. Net. 75 ml 2.5 fl oz (US)